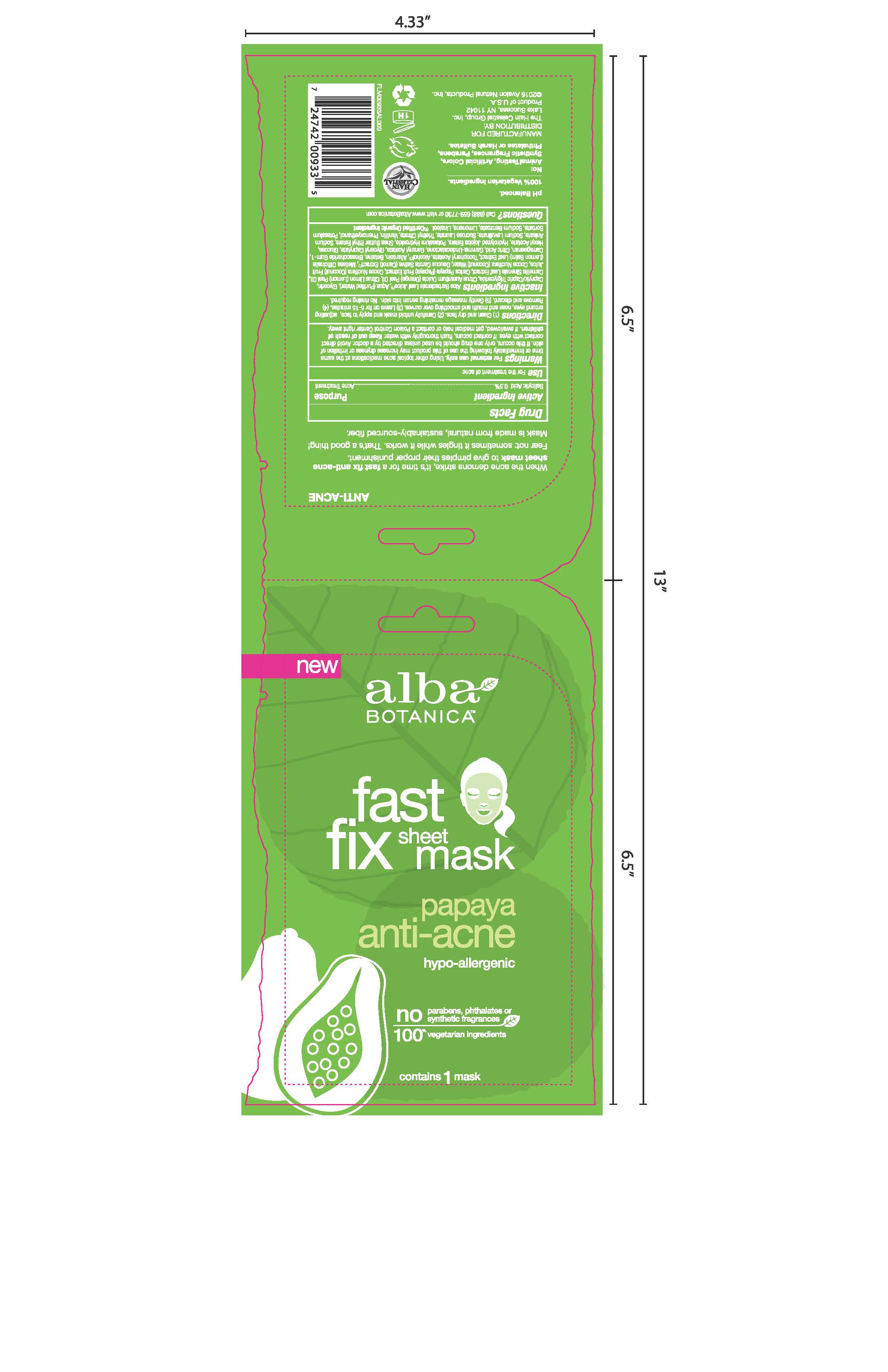 DRUG LABEL: AL00933 Alba Botanica Fast Fix Papaya Anti Acne Sheet Mask
NDC: 61995-2933 | Form: CLOTH
Manufacturer: The Hain Celestial Group, Inc.
Category: otc | Type: HUMAN OTC DRUG LABEL
Date: 20210205

ACTIVE INGREDIENTS: SALICYLIC ACID 2 g/1 1
INACTIVE INGREDIENTS: ALOE VERA LEAF; WATER; GLYCERIN; PAPAYA; COCONUT WATER; MELISSA OFFICINALIS LEAF; BETAINE; BIOSACCHARIDE GUM-1; CARRAGEENAN; CITRIC ACID MONOHYDRATE; .GAMMA.-UNDECALACTONE; SODIUM LEVULINATE; COCONUT JUICE; ALCOHOL; ALLANTOIN; GERANYL ACETATE; HEXYL ACETATE; HYDROLYZED JOJOBA ESTERS (ACID FORM); POTASSIUM HYDROXIDE; SODIUM ANISATE; SUCROSE LAURATE; TRIETHYL CITRATE; VANILLIN; MEDIUM-CHAIN TRIGLYCERIDES; ORANGE OIL; GREEN TEA LEAF; ALPHA-TOCOPHEROL ACETATE; PHENOXYETHANOL; CARROT; DEXTROSE; POTASSIUM SORBATE; SODIUM BENZOATE; LEMON OIL; GLYCERYL MONOCAPRYLATE

Alba Botanica Fast Fix Papaya Anti-Acne Sheet Mask

ACTIVE INGREDIENT

Salicylic Acid - 0.5%

PURPOSE

Acne Treatment

INDICATIONS AND USAGE

For the treatment of acne.

WARNINGS

For external use only. Using other topical acne medications at the same time or immediately following the use of this product may increase dryiness or irritation of skin. If this occurs, only one drug should be used unless directed by a doctor. Avoid direct contact wit eyes. If the contact occurs, flush throughly with water.

Keep out of reach of children. If swallowed, get madical help or contact Poison Control Center right away.

INACTIVE INGREDIENT

Aloe Barbadensis Leaf Juice (1), Aqua (Water), Glycerin, Caprylic/Capric triglyceride, Citrus Aurantium Dulcis (Orange) Peel Oil, Citrus Limon (Lemon) Peel Oil, Camellia Sinensis Leaf Extract, Carica Papaya (Papaya) Fruit Extract,Cocos Nucifera (Coconut) Fruit Juice, Cocos Nucifera (Coconut) Water, Daucus Carota Sativa (Carrot) Extract (1), Melissa Officinalis (Lemon Balm) Leaf Extract, Tocopheryl Acetate, Alcohol (1), Allantoin, Betaine, Biosaccharide gum-1,Carrageenan, Citric Acid, Gamma-Undecalactone, Geranyl Acetate, Glyceryl Caprylate, Glucose, Hexyl Acetate, Hydrolyzed Jojoba Esters, Potassium Hydroxide, Shea Butter Ethyl Ester,Sodium Anisate, Sodium Levulinate, Sucrose Laurate, Triethyl Citrate, Vanillin, Phenoxyethanol, Potassium Sorbate, Sodium Benzoate, Limonene, Linalool.

(1) Certified Organic Ingredient

QUESTIONS

Questions? Call (888)-659-7730 or visit www.AlbaBotanica.com

DOSAGE AND ADMINISTRATION

1. Clean and dry face. 2. Carefully unfold mask and apply to face, adjusting around eyes, nose and mouth and smoothing over curves. 3. Leave on for 5-15 minutes. 4. Remove and discard. 5.Gentle massage remaining serum into skin. No rinsing required.